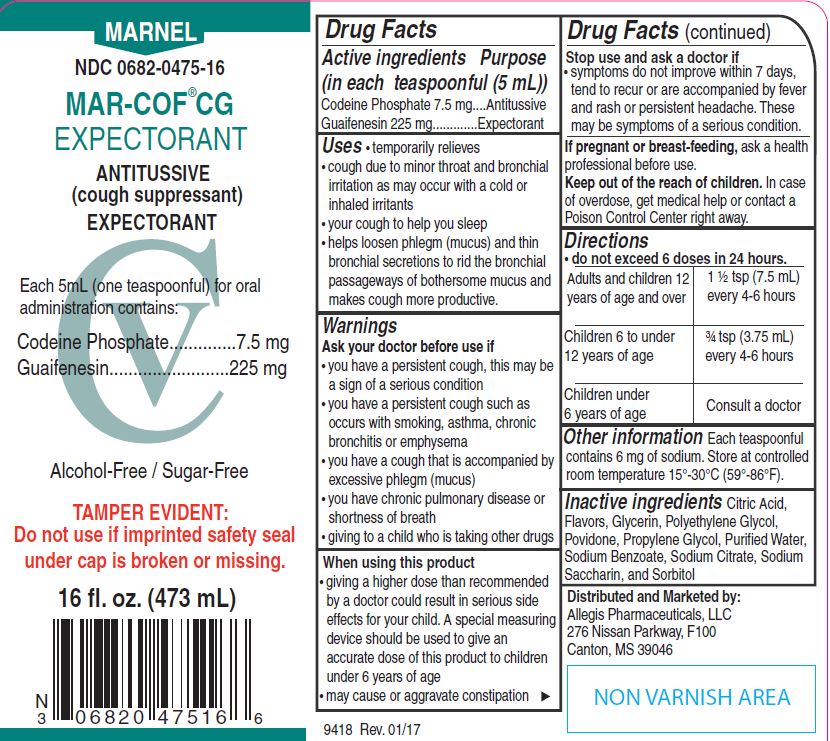 DRUG LABEL: MAR-COF CG
NDC: 0682-0475 | Form: SYRUP
Manufacturer: Marnel Pharmaceuticals, LLC
Category: otc | Type: HUMAN OTC DRUG LABEL
Date: 20240315
DEA Schedule: CV

ACTIVE INGREDIENTS: CODEINE PHOSPHATE 7.5 mg/5 mL; GUAIFENESIN 225 mg/5 mL
INACTIVE INGREDIENTS: CITRIC ACID MONOHYDRATE; GLYCERIN; POLYETHYLENE GLYCOL, UNSPECIFIED; POVIDONE, UNSPECIFIED; PROPYLENE GLYCOL; WATER; SODIUM BENZOATE; SODIUM CITRATE, UNSPECIFIED FORM; SACCHARIN SODIUM; SORBITOL

MAR-COF® CG
Expectorant

Drug Facts

ACTIVE INGREDIENT

Active ingredients (in each teaspoonful (5 mL)) | Purpose
Codeine Phosphate 7.5 mg | Antitussive
Guaifenesin 225 mg | Expectorant

Uses

- temporarily relieves
  - cough due to minor throat and bronchial irritation as may occur with a cold or inhaled irritants
  - your cough to help you sleep
  - helps loosen phlegm (mucus) and thin bronchial secretions to rid the bronchial passageways of bothersome mucus and makes cough more productive.

Warnings

Ask your doctor before use if

- you have a persistent cough, this may be a sign of a serious condition
- you have a persistent cough such as occurs with smoking, asthma, chronic bronchitis or emphysema
- you have a cough that is accompanied by excessive phlegm (mucus)
- you have chronic pulmonary disease or shortness of breath
- giving to a child who is taking other drugs

When using this product

- giving a higher dose than recommended by a doctor could result in serious side effects for your child. A special measuring device should be used to give an accurate dose of this product to children under 6 years of age
- may cause or aggravate constipation

Stop use and ask a doctor if

- symptoms do not improve within 7 days, tend to recur or are accompanied by fever and rash or persistent headache. These may be symptoms of a serious condition.

PREGNANCY OR BREAST FEEDING

If pregnant or breast-feeding, ask a health professional before use.

KEEP OUT OF REACH OF CHILDREN

Keep out of the reach of children. In case of overdose, get medical help or contact a Poison Control Center right away.

Directions

- do not exceed 6 doses in 24 hours.

Adults and children 12 years of age and over | 1 ½ tsp (7.5 mL) every 4-6 hours
Children 6 to under 12 years of age | ¾ tsp (3.75 mL) every 4-6 hours
Children under 6 years of age | Consult a doctor

Other information

Each teaspoonful contains 6 mg of sodium. Store at controlled room temperature 15°-30°C (59°-86°F).

Inactive ingredients

Citric Acid, Flavors, Glycerin, Polyethylene Glycol, Povidone, Propylene Glycol, Purified Water, Sodium Benzoate, Sodium Citrate, Sodium Saccharin, and Sorbitol

Distributed and Marketed By:

Allegis Pharmaceuticals, LLC

276 Nissan Parkway, F100

Canton, MS 39046

PRINCIPAL DISPLAY PANEL - 473 mL Bottle Label

MARNEL

NDC 0682-0475-16

MAR-COF®CG
EXPECTORANT

ANTITUSSIVE
(cough suppressant)
EXPECTORANT

Each 5mL (one teaspoonful) for oral
administration contains:

Codeine Phosphate 7.5 mg
Guaifenesin 225 mg

Alcohol-Free / Sugar-Free

TAMPER EVIDENT:
Do not use if imprinted safety seal
under cap is broken or missing.

16 fl. oz. (473 mL)